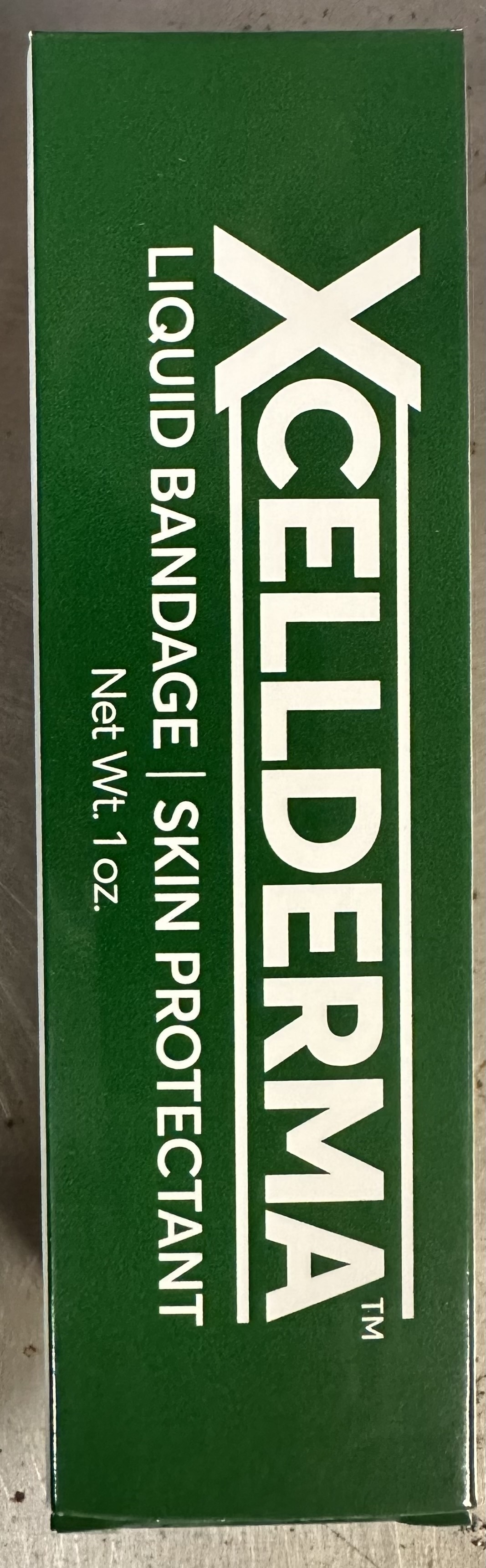 DRUG LABEL: Xcellderma
NDC: 84076-111 | Form: CREAM
Manufacturer: Regenerex Pharma INC
Category: otc | Type: HUMAN OTC DRUG LABEL
Date: 20250514

ACTIVE INGREDIENTS: ZINC ACETATE 0.001 g/1 g
INACTIVE INGREDIENTS: CALCIUM CHLORIDE ANHYDROUS; RUBIDIUM CHLORIDE; POLYETHYLENE GLYCOL 4000; ZINC CHLORIDE 0.002 g/1 g; ANHYDROUS CITRIC ACID; WATER; POTASSIUM CITRATE ANHYDROUS; POLYETHYLENE GLYCOL 400

DOSAGE AND ADMINISTRATION

Clean the affected area. Apply Xcellderma. Reapply after 24 hours.

WARNINGS

Warnings: External use only. Avoid contact with eyes. Not to be applied over deep or puncture wounds, infections or lacerations. If condition worsens or does not improve within 7 days, stop use and consult a doctor.

INDICATIONS AND USAGE

Indications: To cover and protect abrasions, skin tears, pressure ulcers and minor burns.

INACTIVE INGREDIENT

Inactive ingredients: Polyethylene Glycol 4000, Polyethylene Glycol 400, Water, Citric Acid, Potassium Citrate, Benzoic Acid, Rubidium Chloride, Calcium Chloride.

Keep out of reach of children.

PURPOSE

To serve as a wound protectant